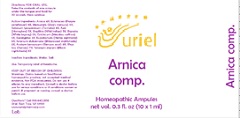 DRUG LABEL: Arnica comp.
NDC: 48951-1339 | Form: LIQUID
Manufacturer: Uriel Pharmacy Inc.
Category: homeopathic | Type: HUMAN OTC DRUG LABEL
Date: 20201217

ACTIVE INGREDIENTS: ECHINACEA, UNSPECIFIED 4 [hp_X]/1 mL; BAPTISIA AUSTRALIS ROOT 5 [hp_X]/1 mL; SOLANUM DULCAMARA FLOWER 5 [hp_X]/1 mL; SOLANUM NIGRUM FRUIT 8 [hp_X]/1 mL; MERCURIALIS PERENNIS 4 [hp_X]/1 mL; ARNICA MONTANA 4 [hp_X]/1 mL; SOLANUM LYCOPERSICUM FRUITING TOP 4 [hp_X]/1 mL; APIS MELLIFERA 5 [hp_X]/1 mL; EUCALYPTUS GUM 5 [hp_X]/1 mL; COLCHICUM AUTUMNALE WHOLE 5 [hp_X]/1 mL; BRYONIA ALBA ROOT 5 [hp_X]/1 mL; EUPATORIUM CANNABINUM FLOWERING TOP 5 [hp_X]/1 mL; BENZOIC ACID 6 [hp_X]/1 mL; TOXICODENDRON PUBESCENS LEAF 7 [hp_X]/1 mL
INACTIVE INGREDIENTS: SODIUM CHLORIDE; WATER

Arnica comp.

INDICATIONS AND USAGE

Directions: FOR ORAL USE.

DOSAGE AND ADMINISTRATION

Take the contents of one ampule under the tongue and hold for 30 seconds, then swallow.

ACTIVE INGREDIENT

Active Ingredients: Arnica 4X, Echinacea (Purple coneflower) 4X, Mercurialis (Dog’s mercury) 4X, Solanum lycopersicum (Tomato) 4X, Apis (Honeybee) 5X, Baptisia (Wild indigo) 5X, Bryonia (White bryony) 5X, Colchicum (Meadow saffron) 5X, Eucalyptus 5X, Eupatorium (Hemp agrimony) 5X, Solanum dulcamara (Bittersweet nightshade) 5X, Acidum benzoicum (Benzoic acid) 6X, Rhus tox. (Sumac) 7X, Solanum nigrum (Black nightshade) 8X

Inactive Ingredients: Water, Salt

PURPOSE

Use: Temporary relief of headache.

KEEP OUT OF REACH OF CHILDREN.

WARNINGS

Warnings: Claims based on traditional homeopathic practice, not accepted medical evidence. Not FDA evaluated. Do not use if allergic to any ingredient. Consult a doctor before use for serious conditions or if conditions worsen or persist. If pregnant or nursing, consult a doctor before use.

Questions? Call 866.642.2858
Uriel, East Troy, WI 53120
www.urielpharmacy.com

Lot: